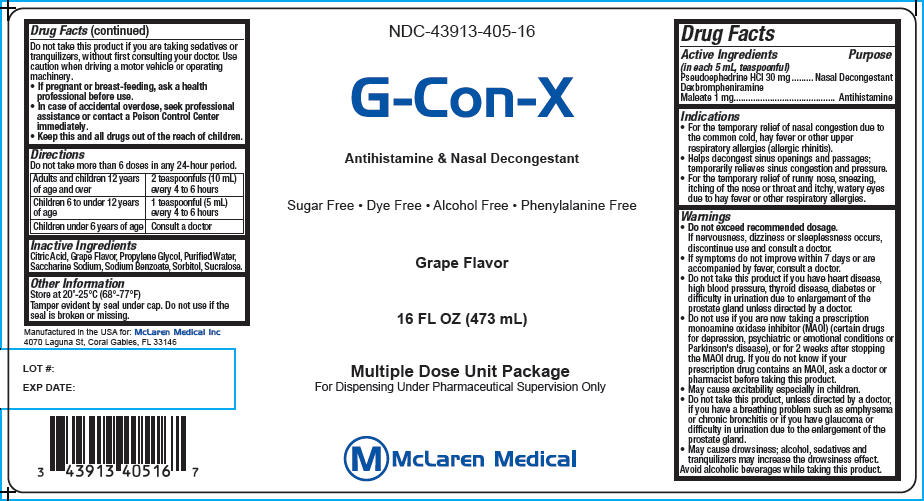 DRUG LABEL: G-Con-X
NDC: 43913-405 | Form: LIQUID
Manufacturer: McLaren Medical
Category: otc | Type: HUMAN OTC DRUG LABEL
Date: 20140423

ACTIVE INGREDIENTS: Dexbrompheniramine Maleate 1 mg/5 mL; Pseudoephedrine Hydrochloride 30 mg/5 mL
INACTIVE INGREDIENTS: Sodium Benzoate; Citric Acid Monohydrate; Sorbitol; Saccharin Sodium; Sucralose; Propylene Glycol; Water

G-Con-X

Drug Facts

ACTIVE INGREDIENT

Active Ingredients (in each 5 mL, teaspoonful) | Purpose
Pseudoephedrine HCl 30 mg | Nasal Decongestant
Dexbrompheniramine Maleate 1 mg | Antihistamine

Indications

- For the temporary relief of nasal congestion due to the common cold, hay fever or other upper respiratory allergies (allergic rhinitis).
- Helps decongest sinus openings and passages; temporarily relieves sinus congestion and pressure.
- For the temporary relief of runny nose, sneezing, itching of the nose or throat and itchy, watery eyes due to hay fever or other respiratory allergies.

Warnings

ASK DOCTOR

- Do not exceed recommended dosage.
  If nervousness, dizziness or sleeplessness occurs, discontinue use and consult a doctor.
- If symptoms do not improve within 7 days or are accompanied by fever, consult a doctor.

DO NOT USE

- Do not take this product if you have heart disease, high blood pressure, thyroid disease, diabetes or difficulty in urination due to enlargement of the prostate gland unless directed by a doctor.
- Do not use if you are now taking a prescription monoamine oxidase inhibitor (MAOI) (certain drugs for depression, psychiatric or emotional conditions or Parkinson's disease), or for 2 weeks after stopping the MAOI drug. If you do not know if your prescription drug contains an MAOI, ask a doctor or pharmacist before taking this product.

WHEN USING

- May cause excitability especially in children.

DO NOT USE

- Do not take this product, unless directed by a doctor, if you have a breathing problem such as emphysema or chronic bronchitis or if you have glaucoma or difficulty in urination due to the enlargement of the prostate gland.

WHEN USING

- May cause drowsiness; alcohol, sedatives and tranquilizers may increase the drowsiness effect.

Avoid alcoholic beverages while taking this product.

DO NOT USE

Do not take this product if you are taking sedatives or tranquilizers, without first consulting your doctor. Use caution when driving a motor vehicle or operating machinery.

PREGNANCY OR BREAST FEEDING

- If pregnant or breast-feeding, ask a health professional before use.

ASK DOCTOR/PHARMACIST

- In case of accidental overdose, seek professional assistance or contact a Poison Control Center immediately.

KEEP OUT OF REACH OF CHILDREN

- Keep this and all drugs out of the reach of children.

Directions

Do not take more than 6 doses in any 24-hour period.

Adults and children 12 years of age and over | 2 teaspoonfuls (10 mL) every 4 to 6 hours
Children 6 to under 12 years of age | 1 teaspoonful (5 mL) every 4 to 6 hours
Children under 6 years of age | Consult a doctor

Inactive Ingredients

Citric Acid, Grape Flavor, Propylene Glycol, Purified Water, Saccharine Sodium, Sodium Benzoate, Sorbitol, Sucralose.

Other Information

Store at 20°-25°C (68°-77°F)

Tamper evident by seal under cap. Do not use if the seal is broken or missing.

PRINCIPAL DISPLAY PANEL - 473 mL Bottle Label

NDC-43913-405-16

G-Con-X

Antihistamine & Nasal Decongestant

Sugar Free • Dye Free • Alcohol Free • Phenylalanine Free

Grape Flavor

16 FL OZ (473 mL)

Multiple Dose Unit Package
For Dispensing Under Pharmaceutical Supervision Only

McLaren Medical